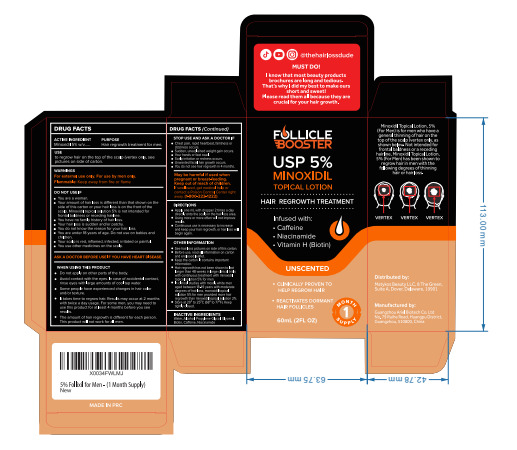 DRUG LABEL: Follicle  Follixil 5% Minoxidil Hair Regrowth-Lotion
NDC: 84148-005 | Form: LIQUID
Manufacturer: Guangzhou Ariel Biotech Co., Ltd.
Category: otc | Type: HUMAN OTC DRUG LABEL
Date: 20240417

ACTIVE INGREDIENTS: MINOXIDIL 5 mg/100 mL
INACTIVE INGREDIENTS: GLYCERIN; BIOTIN; NIACINAMIDE; CAFFEINE; WATER; ALCOHOL; PROPYLENE GLYCOL

Active Ingredient(s)

Minoxidil 5%

Purpose

Hair regrowth treatment for men.

Use

to regrow hair on the top of the scalp (vertex only, see pictures on side of carton.

Warnings

For external use only. For use by men only.

Flammable: Keep away from fire or flame

Do not use

●You are a woman.
●Your amount of hair loss is different than that shown on the side of this carton or your hair loss is on the front of the
scalp. Minoxidil topical solution 5% is not intended for frontal baldness or receding hairline.
●You have no family history of hair loss.
●Your hair loss is sudden and/or patchy.
●You do not know the reason for your hair loss.
●You are under 18 years of age. Do not use on babies and children.
●Your scalp is red, inflamed, infected, iritated or painful.
●You use other medicines on the scalp.

WHEN USING

●Do not apply on other parts of the body.
●Avoid contact with the eyes. In case of accidental contact, rinse eyes with large amounts of cool tap water.
●Some people have experienced changes in hair color and/or texture.
●It takes time to regrow hair. Results may occur at 2 months with twice a day usage. For some men, you may need to
use this product for at least 4 months before you see results.
●The amount of hair regrowth is different for each person. This product will not work for all men.

STOP USE

●Chest pain, rapid heartbeat, faintness or dizziness occurs.
●Sudden, unexplained weight gain occurs.
●Your hands or feet swell.
●Scalp iritation or redness occurs.
●Unwanted facial hair growth occurs.
●You do not see hair regrowth in 4 months.

KEEP OUT OF REACH OF CHILDREN

May be harmful if used when pregnant or breast-feeding. Keep out of reach of children.
If swallowed, get medical help or contact a Poison Control Center right away. (1-800-222-1222)

Directions

●Apply one mL with dropper 2 times a day directly onto the scalp in the hair loss area.
●Using more or more often will not improve results.
●Continuous use is necessary to increase and keep your hair regrowth, or hair loss will begin again.

Other information

1.See hair loss pictures on side of this carton.
2.Before use, read all information on carton and enclosed leaflet.
3.Keep the carton. It contains important information.
4.Hair regrowth has not been shown to last longer than 48 weeks in large clinical trials with continuous treatment with minoxidil
topical solution 5% for men.
5.In clinical studies with mostly white men aged between 18-49 years with moderate degrees of hair loss, monoxidil topical
solution 5% for men provided more hair regrowth than minoxidil topical solution 2%，
6.Store at 20° to 259C (68° to 77°F). Keep tightly closed.

Inactive ingredients

Water, Alcohol, Propylene Glycol, Glycerol, Biotin, Caffeine, Niacinamide